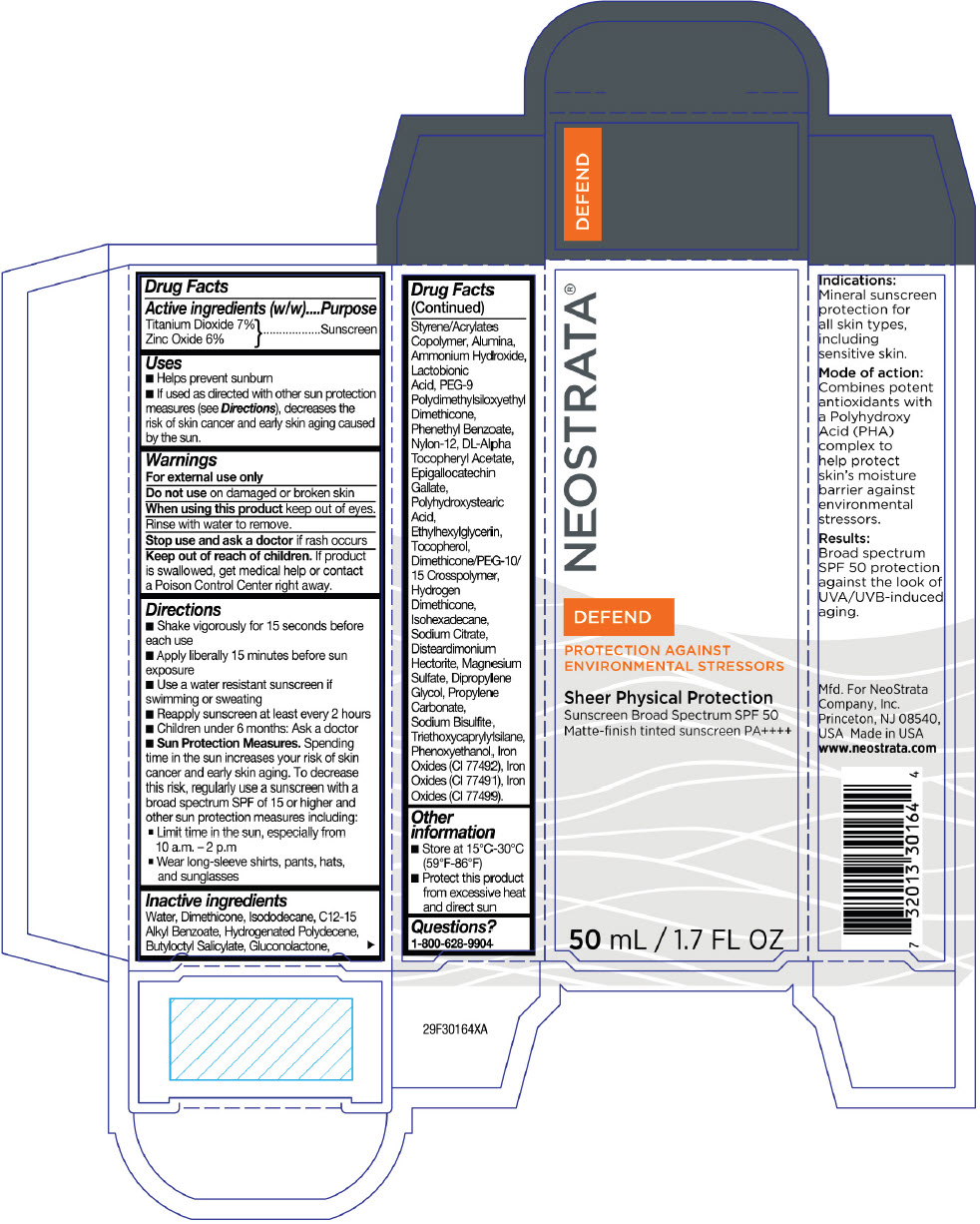 DRUG LABEL: NeoStrata Sheer Physical Protection
NDC: 58414-0018 | Form: LOTION
Manufacturer: NeoStrata Company Inc.
Category: otc | Type: HUMAN OTC DRUG LABEL
Date: 20250110

ACTIVE INGREDIENTS: TITANIUM DIOXIDE 70 mg/1 mL; ZINC OXIDE 60 mg/1 mL
INACTIVE INGREDIENTS: WATER; DIMETHICONE; ISODODECANE; ALKYL (C12-15) BENZOATE; HYDROGENATED POLYDECENE TYPE I; BUTYLOCTYL SALICYLATE; GLUCONOLACTONE; ALUMINUM OXIDE; AMMONIA; LACTOBIONIC ACID; PEG-9 POLYDIMETHYLSILOXYETHYL DIMETHICONE; PHENETHYL BENZOATE; NYLON-12; .ALPHA.-TOCOPHEROL ACETATE; EPIGALLOCATECHIN GALLATE; POLYHYDROXYSTEARIC ACID (2300 MW); ETHYLHEXYLGLYCERIN; ISOHEXADECANE; TOCOPHEROL; DIMETHICONE/PEG-10/15 CROSSPOLYMER; DIPROPYLENE GLYCOL; DISTEARDIMONIUM HECTORITE; MAGNESIUM SULFATE, UNSPECIFIED FORM; PROPYLENE CARBONATE; SODIUM CITRATE, UNSPECIFIED FORM; TRIETHOXYCAPRYLYLSILANE; SODIUM BISULFITE; PHENOXYETHANOL; FERRIC OXIDE RED; FERRIC OXIDE YELLOW; FERROSOFERRIC OXIDE

NeoStrata®Sheer Physical Protection

Drug Facts

Active ingredients (w/w)

Titanium Dioxide 7%
Zinc Oxide 6%

Purpose

Sunscreen

Uses

- Helps prevent sunburn
- If used as directed with other sun protection measures (see Directions), decreases the risk of skin cancer and early skin aging caused by the sun.

Warnings

For external use only

Do not use on damaged or broken skin

WHEN USING

When using this productkeep out of eyes. Rinse with water to remove.

Stop use and ask a doctorif rash occurs

Keep out of reach of children.If product is swallowed, get medical help or contact a Poison Control Center right away.

Directions

- Shake vigorously for 15 seconds before each use
- Apply liberally 15 minutes before sun exposure
- Use a water resistant sunscreen if swimming or sweating
- Reapply sunscreen at least every 2 hours
- Children under 6 months: Ask a doctor
- Sun Protection Measures.Spending time in the sun increases your risk of skin cancer and early skin aging. To decrease this risk, regularly use a sunscreen with a broad spectrum SPF of 15 or higher and other sun protection measures including:
  - Limit time in the sun, especially from 10 a.m.–2 p.m.
  - Wear long-sleeve shirts, pants, hats, and sunglasses

Inactive ingredients

Water, Dimethicone, Isododecane, C12-15 Alkyl Benzoate, Hydrogenated Polydecene, Butyloctyl Salicylate, Gluconolactone, Styrene/Acrylates Copolymer, Alumina, Ammonium Hydroxide, Lactobionic Acid, PEG-9 Polydimethylsiloxyethyl Dimethicone, Phenethyl Benzoate, Nylon-12, DL-Alpha Tocopheryl Acetate, Epigallocatechin Gallate, Polyhydroxystearic Acid, Ethylhexylglycerin, Tocopherol, Dimethicone/PEG-10/ 15 Crosspolymer, Hydrogen Dimethicone, Isohexadecane, Sodium Citrate, Disteardimonium Hectorite, Magnesium Sulfate, Dipropylene Glycol, Propylene Carbonate, Sodium Bisulfite, Triethoxycaprylylsilane, Phenoxyethanol, Iron Oxides (CI 77492), Iron Oxides (CI 77491), Iron Oxides (CI 77499).

Other information

- Store at 15°C-30°C (59°F-86°F)
- Protect this product from excessive heat and direct sun

Questions?

1-800-628-9904

PRINCIPAL DISPLAY PANEL - 50 mL Bottle Carton

NEOSTRATA®

DEFEND
PROTECTION AGAINST
ENVIRONMENTAL STRESSORS

Sheer Physical Protection
Sunscreen Broad Spectrum SPF 50
Matte-finish tinted sunscreen PA++++

50 mL / 1.7 FL OZ